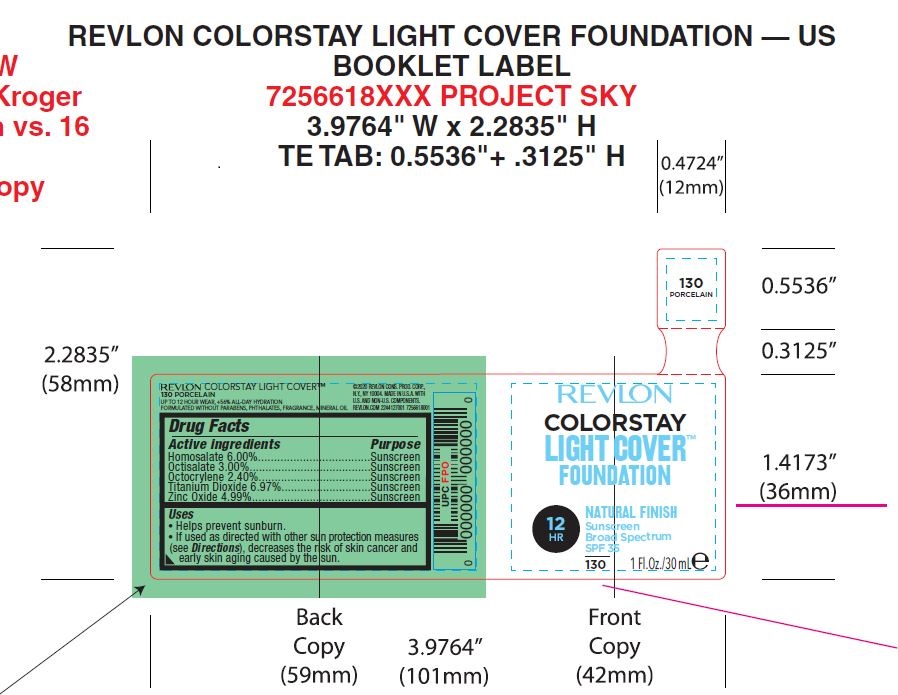 DRUG LABEL: Revlon Colorstay Light Cover Foundation
NDC: 10967-663 | Form: EMULSION
Manufacturer: Revlon
Category: otc | Type: HUMAN OTC DRUG LABEL
Date: 20240112

ACTIVE INGREDIENTS: TITANIUM DIOXIDE 6.97 mg/1 mL; ZINC OXIDE 4.99 mg/1 mL; HOMOSALATE 6 mg/1 mL; OCTISALATE 3 mg/1 mL; OCTOCRYLENE 2.4 mg/1 mL
INACTIVE INGREDIENTS: POLYGLYCERYL-3 DIISOSTEARATE; PROPYLENE CARBONATE; EDETATE SODIUM; METHYL METHACRYLATE; GLYCERIN; DIMETHICONE/VINYL DIMETHICONE CROSSPOLYMER (HARD PARTICLE); ALUMINUM OXIDE; PHENYL TRIMETHICONE; PROPANEDIOL; NIACINAMIDE; PEG/PPG-18/18 DIMETHICONE; CAFFEINE; DIMETHICONOL (14000 CST); METHICONE (20 CST); DISTEARDIMONIUM HECTORITE; PUNICA GRANATUM SEED OIL; DIMETHICONE 100; PEG-10 DIMETHICONE (600 CST); ALCOHOL; CAPRYLYL GLYCOL; DIMETHICONE/VINYL DIMETHICONE CROSSPOLYMER (SOFT PARTICLE); SILICON DIOXIDE; 1,2-HEXANEDIOL; DIMETHICONE 1000; HYDROGEN DIMETHICONE (13 CST); ISOCETETH-10; LECITHIN, SOYBEAN; MAGNESIUM SULFATE ANHYDROUS; MICA; .ALPHA.-TOCOPHEROL ACETATE; WATER; TRIMETHYLSILOXYSILICATE (M/Q 0.6-0.8); CYCLOMETHICONE 5; ISODODECANE; TRIETHOXYCAPRYLYLSILANE

Revlon Colorstay Light Cover Foundation

Uses

Helps prevent Sunburn

If used as directed with other sun protection measures, decreases the risk of skin cancer and early skin aging caused by the sun

Warnings

For external use only.

Do not use on damaged or broken skin

When using this product keep out of the eyes. Rinse with water to remove.

Stop use and ask doctor is rash occurs.

KEEP OUT OF REACH OF CHILDREN

If product is swallowed, get medical help or contact Poison Control Center right away.

Active Ingredients

Homosalate 6.00%

Octisalate 3.00%

Octocrylene 2.40%

Titanium Dioxide 6.97%

Zinc Oxide 4.99%

Directions

Apply liberally 15 minutes before sun exposure

Use water resistant sunscreen if swimming or sweating

Repply at least every 2 hours

Children under 6 months: Ask a doctor

Sun Protection Measures

Spending time in the sun increases your risk of skin cancer and early skin aging. To decrease this risk, regularly use a sunscreen with a Broad Spectrum SPF value of 15 or higher and other sun protection measures, including: Limit time in the sun, especially from 10am-2pm, wear long-sleeved shirts, pants, hats and sunglasses.

INACTIVE INGREDIENT

Isododecane, Aqua/Water/Eau, Trimethylsiloxysilicate, Titanium Dioxide, Homosalate,
Zinc Oxide [nano], Dimethicone, Cyclopentasiloxane, Glycerin, Propanediol, Ethylhexyl Salicylate,
PEG-10 Dimethicone, Dimethicone/Vinyl Dimethicone Crosspolymer, Octocrylene, Niacinamide,
PEG/PPG-18/18 Dimethicone, Alumina, Methyl Methacrylate Crosspolymer, Punica Granatum Sterols,
Phenyl Trimethicone, 1,2-Hexanediol, Alcohol Denat., Caffeine, Caprylyl Glycol, Dimethicone
Crosspolymer, Dimethiconol, Disteardimonium Hectorite, Hydrogen Dimethicone, Isoceteth-10,
Lecithin, Magnesium Sulfate, Methicone, Mica, Polyglyceryl-3 Diisostearate, Polysilicone-11,
Propylene Carbonate, Silica, Silica silylate, Tetrasodium EDTA, Tocopheryl Acetate,
Triethoxycaprylylsilane, Iron Oxides (CI 77491), Iron Oxides (CI 77492), Iron Oxides (CI 77499), Titanium Dioxide (CI 77891).

DOSAGE AND ADMINISTRATION

As Needed

INDICATIONS AND USAGE

- Helps prevent sunburn